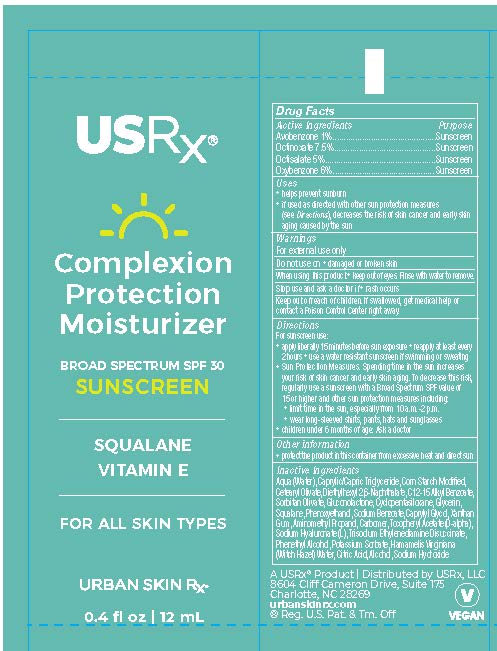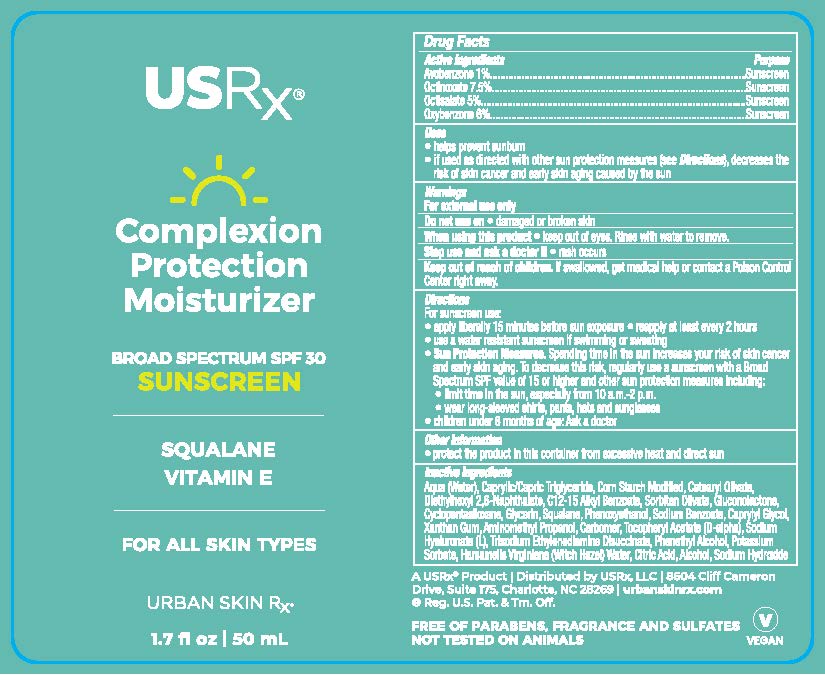 DRUG LABEL: Complexion Protection Moisturizer SPF
NDC: 70809-1902 | Form: CREAM
Manufacturer: USRX LLC
Category: otc | Type: HUMAN OTC DRUG LABEL
Date: 20241001

ACTIVE INGREDIENTS: OCTISALATE 5 mg/100 mL; OCTINOXATE 7.5 mg/100 mL; AVOBENZONE 1 mg/100 mL; BENZOPHENONE 3.6 mg/100 mL
INACTIVE INGREDIENTS: XANTHAN GUM; CARBOXYPOLYMETHYLENE; SODIUM BENZOATE; CAPRYLYL GLYCOL; TRISODIUM ETHYLENEDIAMINE DISUCCINATE; POTASSIUM SORBATE; AMINOMETHYLPROPANOL; PHENYLETHYL ALCOHOL; STARCH, CORN; WATER; CETEARYL OLIVATE; DIETHYLHEXYL 2,6-NAPHTHALATE; HYALURONATE SODIUM; .ALPHA.-TOCOPHEROL ACETATE, D-; CYCLOMETHICONE 5; GLYCERIN; SQUALANE; GLUCONOLACTONE; SORBITAN OLIVATE; ALKYL (C12-15) BENZOATE; MEDIUM-CHAIN TRIGLYCERIDES; PHENOXYETHANOL

Complexion Protection Moisturizer SPF 30

PACKAGE LABEL

ACTIVE INGREDIENT -

Benzophenone 3.6%

Avobenzone 1%

Octinoxate 7.5%

Octisalate 5%

PURPOSE

Sunscreen

WARNINGS

FOR EXTERNAL USE ONLY

DO NOT USE - On damaged or broken skin

STOP USE AND ASK A DOCTOR IF A RASH OCCURRS

INACTIVE INGREDIENT

Aqua (Water), Caprylic/Capric Triglyceride, Corn Starch Modified, Cetearyl Olivate, Diethylhexyl 2,6-Naphthalate, C12-15 Alkyl Benzoate, Sorbitan Olivate, Gluconolactone, Squalane, Glycerin, Cyclopentasiloxane, Tocopheryl Acetate (D-alpha), Sodium Hyaluronate (L), Xanthan Gum, Carbomer, Aminomethyl Propanol, Sodium Benzoate, Phenethyl Alcohol, Caprylyl Glycol, Phenoxyethanol, Trisodium Ethylenediamine Disuccinate, Potassium Sorbate